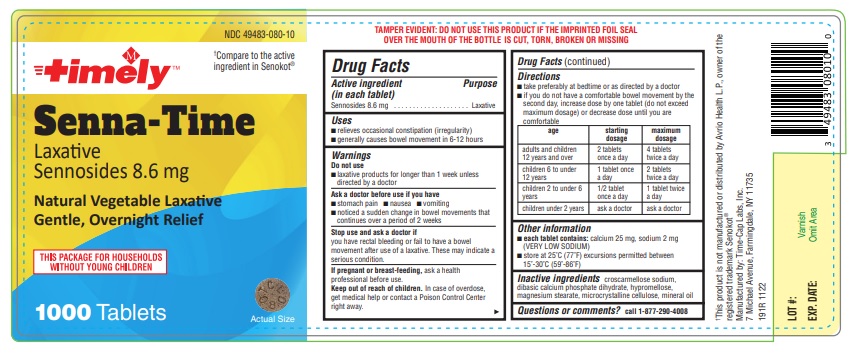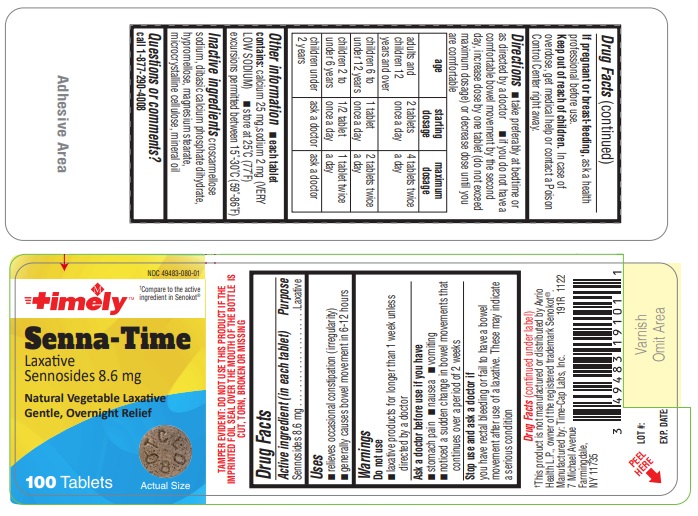 DRUG LABEL: SENNA TIME
NDC: 49483-080 | Form: TABLET, COATED
Manufacturer: TIME CAP LABORATORIES, INC
Category: otc | Type: HUMAN OTC DRUG LABEL
Date: 20250208

ACTIVE INGREDIENTS: SENNOSIDES A AND B 8.6 mg/1 1
INACTIVE INGREDIENTS: DIBASIC CALCIUM PHOSPHATE DIHYDRATE; HYPROMELLOSES; MAGNESIUM STEARATE; MICROCRYSTALLINE CELLULOSE; MINERAL OIL; CROSCARMELLOSE SODIUM

191R Timely 49483 080 Sennosides 8.6 mg Tablets

Active ingredient (in each tablet)
Sennosides 8.6 mg

Purpose
Laxative

Uses

- relieves occasional constipation (irregularity)
- generally causes bowel movement in 6-12 hours

Warnings

Do not use

- laxative products for longer than 1 week unless directed by a doctor

Ask a doctor before use if you have

- stomach pain
- nausea
- vomiting
- noticed a sudden change in bowel movements that continues over a period of 2 weeks

Stop use and ask a doctor if
you have rectal bleeding or fail to have a bowel movement after use of a laxative. These may indicate a serious condition

PREGNANCY OR BREAST FEEDING

If pregnant or breast-feeding, ask a health professional before use.

Keep out of reach of children. In case of overdose, get medical help or contact a Poison Control Center right away.

Directions

- take preferably at bedtime or as directed by a doctor
- if you do not have a comfortable bowel movement by the second day, increase dose by one tablet (do not exceed maximum dosage) or decrease dose until you are comfortable
  age | starting dosage | maximum dosage
  adults and children 12 years and over | 2 tablets once a day | 4 tablets twice a day
  children 6 to under 12 years | 1 tablet once a day | 2 tablets twice a day
  children 2 to under 6 years | 1/2 tablet once a day | 1 tablet twice a day
  children under 2 years | ask a doctor | ask a doctor

OTHER INFORMATION

- each tablet contains: calcium 25 mg,sodium 2 mg (VERY LOW SODIUM)
- store at 25°C (77°F) excursions permitted between 15°-30°C (59°-86°F)

INACTIVE INGREDIENT

Inactive ingredients croscarmellose sodium, dibasic calcium phosphate dihydrate, hypromellose, magnesium stearate, microcrystalline cellulose, mineral oil

Questions or comments?
call 1-877-290-4008